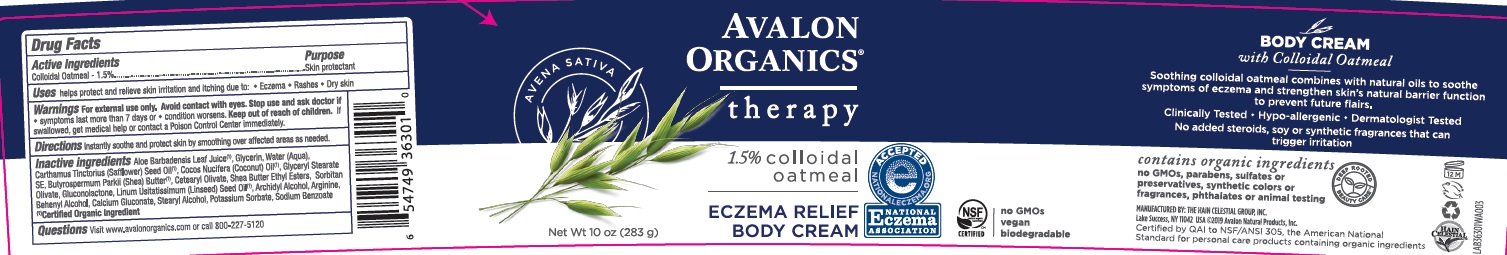 DRUG LABEL: AV3630100 Avalon Organics Eczema Relief Body
NDC: 61995-1301 | Form: CREAM
Manufacturer: The Hain Celestial Group, Inc.
Category: otc | Type: HUMAN OTC DRUG LABEL
Date: 20210412

ACTIVE INGREDIENTS: OATMEAL 1.5 g/100 g
INACTIVE INGREDIENTS: ARACHIDYL ALCOHOL; SAFFLOWER OIL; SHEA BUTTER; CETEARYL OLIVATE; ARGININE; CALCIUM GLUCONATE; COCONUT OIL; ALOE VERA LEAF; GLYCERIN; WATER; GLYCERYL STEARATE SE; SODIUM BENZOATE; GLUCONOLACTONE; LINSEED OIL; STEARYL ALCOHOL; DOCOSANOL; POTASSIUM SORBATE; SORBITAN OLIVATE

Avalon Organics Eczema Therapy Cream

Active Ingredient

Colloidal Oatmeal - 1.5%

DOSAGE AND ADMINISTRATION

Massage cleanser over damp face and body, rinse clean, pat dry. Following immediately with an Eczema Relief cream locks in moisture.

PURPOSE

Skin Protectant

WARNINGS

For external use only. Avoid contacts with eyes. Stop use and ask a doctor if symptoms last more than 7 days or condition worsens.

Keep out of reach of children. If swallowed get medical help or contact Poison Center immediately.

INACTIVE INGREDIENT

Aloe Barbadensis Leaf Juice(1), Glycerin, Water, Carthamus Tinctorius (Safflower) Oil, Cocos Nucifera (Coconut) Oil (1), Glyceryl Stearate SE, Butyrospermum Parkii(Shea Butter(1), Cetearyl Olivate, Shea Butter Ethyl Esters, Sorbitan Olivate, Gluconolactone, , Linum Usatatissimum (Linseed) Seed Oil (1), Archidyl Alcohol, Arginine, Behenyl Alcohol, Calcium Gluconate, Stearyl Alcohol, Potassium Sorbate, Sodium Benzoate.

(1) Certified Organic Ingredient

INDICATIONS AND USAGE

Helps protect and relieve skin irritation and itching due to: Eczema, Rashes, Dry skin.